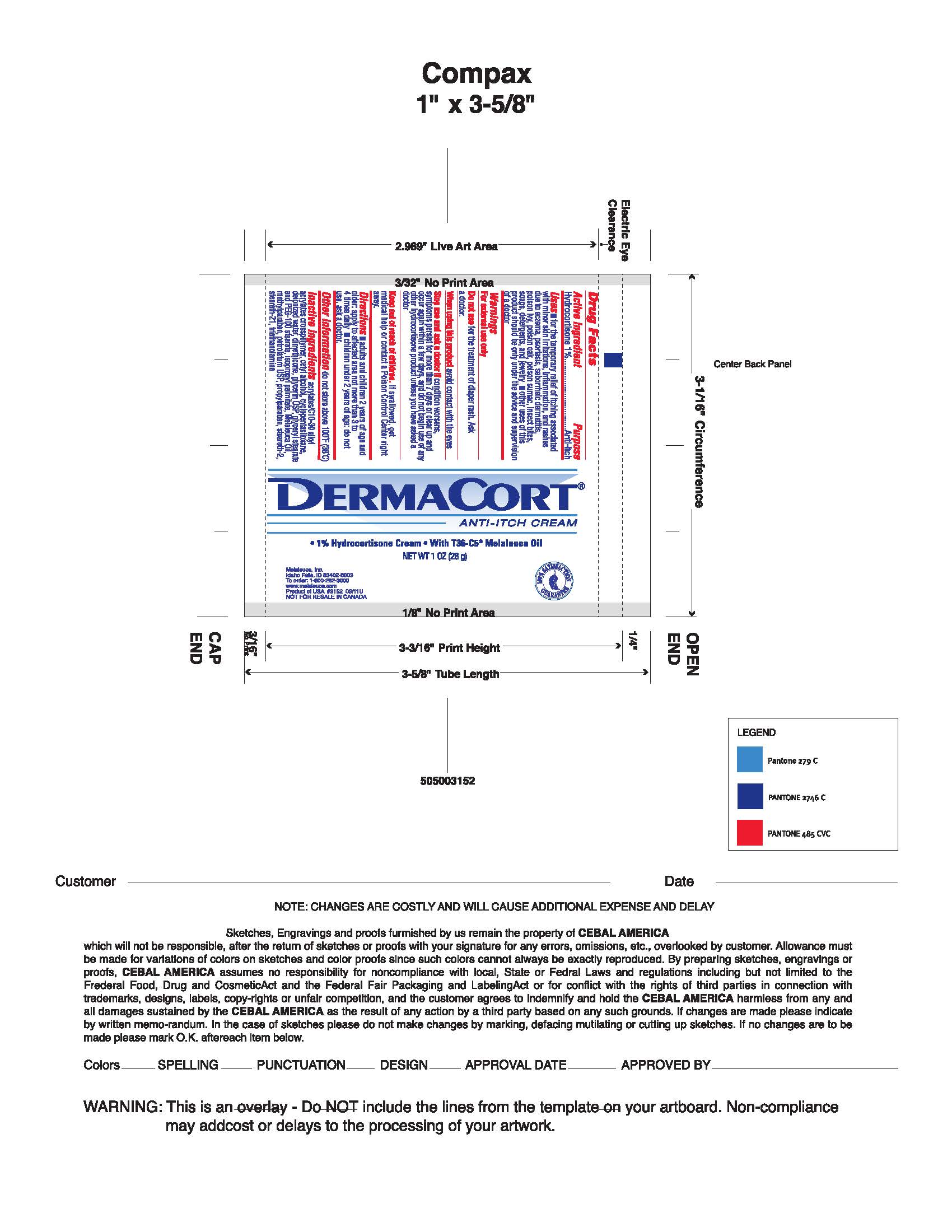 DRUG LABEL: DermaCort
NDC: 54473-117 | Form: CREAM
Manufacturer: Melaleuca, Inc.
Category: otc | Type: HUMAN OTC DRUG LABEL
Date: 20250320

ACTIVE INGREDIENTS: HYDROCORTISONE 10 mg/1 g
INACTIVE INGREDIENTS: POLYOXYL 100 STEARATE; PROPYLPARABEN; STEARETH-2; STEARETH-21; TEA TREE OIL; TROLAMINE; WATER; CARBOMER COPOLYMER TYPE B (ALLYL PENTAERYTHRITOL CROSSLINKED); CETYL ALCOHOL; CYCLOMETHICONE 5; DIMETHICONE; GLYCERIN; GLYCERYL MONOSTEARATE; ISOPROPYL PALMITATE; METHYLPARABEN; PETROLATUM

DermaCort

Active ingredient
Hydrocortisone 1%

Purpose
Anti-itch

Uses

- For the temporary relief of itching associated with minor skin irritations, inflammation and rashes due to eczema, psoriasis, , seborrheic dermatitis, poison ivy, poison oak, poison sumac, insect bites, soaps, detergents, and jewelery
- Other use of this product should be only under the advice and supervision of a doctor.

Warnings
For external use only.

When using this product avoid contact with the eyes.

Stop use and ask a doctor if conditions worsens, or if symptoms persist for more than 7 days or clear up and occur again within a few days, stop use of this product and do not begin use of any other hydrocortisone product unless you have consulted a doctor.

Do not use for the treatment of diaper rash. Consult a doctor.

Keep out of reach of children.
In case of accidental ingestion, seek professional assistance or contact a Poison Control Center immediately.

DOSAGE AND ADMINISTRATION

Directions adults and children 2 years of age and older: Apply to affected area not more than 3 to 4 times daily. Children under 2 years of age: Do not use, consult a doctor.

Other information Do not store above 100°F.

INACTIVE INGREDIENT

Inactive ingredients Acrylates/C10-30 Alkyl Acrylates Crosspolymer, Cetyl Alcohol, Cyclopentasiloxane, Deionized Water, Dimethicone, Glycerin USP, Glyceryl Stearate and PEG-100 Stearate, Isopropyl Palmitate, Melaleuca Oil, Methylparaben, Petrolatum USP, Propylparaben, Serareth-2, Steareth-21, Triethanolamine.